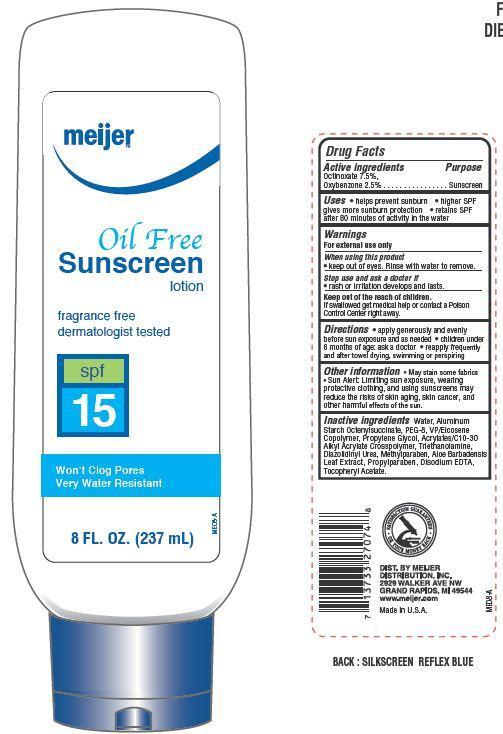 DRUG LABEL: Meijer Oil Free SPF 15
NDC: 41250-030 | Form: LOTION
Manufacturer: Meijer Distribution Inc
Category: otc | Type: HUMAN OTC DRUG LABEL
Date: 20130701

ACTIVE INGREDIENTS: OCTINOXATE 7.5 g/100 g; OXYBENZONE 2.5 g/100 g
INACTIVE INGREDIENTS: WATER; ALUMINUM STARCH OCTENYLSUCCINATE; POLYETHYLENE GLYCOL 400; PROPYLENE GLYCOL; TROLAMINE; DIAZOLIDINYL UREA; METHYLPARABEN; ALOE VERA LEAF; PROPYLPARABEN; EDETATE DISODIUM; .ALPHA.-TOCOPHEROL ACETATE

Drug Facts

Active ingredients

Octinoxate 7.5%

Oxybenzone 2.5%

Uses

- helps prevent suburn
- higher SPF gives more sunburn protection
- retains SPF after 80 minutes of activity in water

Warnings

For external use only

When using this product

- keep out of eyes. Rinse with water to remove

Stop use and ask a doctor if

- rash or irritation develops and lasts

KEEP OUT OF REACH OF CHILDREN

Keep out of the reach of children. If swallowed get medical help or contact a Poison Control Center right away.

Directions

- apply generously and evenly before sun exposure and as needed
- children under 6 months of age: ask a doctor
- reapply frequently and after towel drying, swimming or perspiring

Other information

- may stain some fabrics
- Sun Alert: Limiting sun exposure, wearing protective clothing, and using sunscreens may reduce the risks of skin aging, skin cancer and other harmful effects of the sun

Inactive ingredients

Water, Aluminum Starch Octenylsuccinate, PEG-8, VP/Eicosene Copolymer, Propylene Glycol, Acrylates/C10-30 Alkyl Acrylate Crosspolymer, Triethanolamine, Disodium EDTA, Cocos Nucifera (Coconut) Oil, Mineral Oil, Tocopheryl Acetate, Aloe Barbadensis Leaf Extract, Diazolidinyl Urea, Methylparaben, Propylparaben.

Principal Display Panel

meijer

Oil Free

Sunscreen lotion

fragrance free

dermatologist tested

spf 15

Won't Clog Pores

very water resistant

8 FL. OZ. (237 mL)

Purpose

Sunscreen